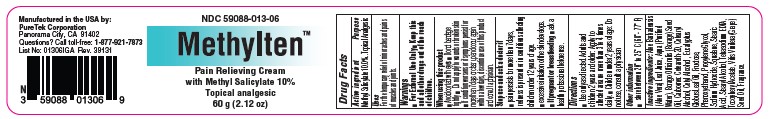 DRUG LABEL: Methylten
NDC: 59088-013 | Form: CREAM
Manufacturer: Puretek Corporation
Category: otc | Type: HUMAN OTC DRUG LABEL
Date: 20250113

ACTIVE INGREDIENTS: METHYL SALICYLATE 1 mg/1 g
INACTIVE INGREDIENTS: PROPYLENE GLYCOL; SODIUM HYDROXIDE; .ALPHA.-TOCOPHEROL ACETATE; STEARIC ACID; AQUA; PHENOXYETHANOL; FRUCTOSE; CETEARYL ALCOHOL; VITIS VINIFERA (GRAPE) SEED OIL; CARBOMER; CETYL ALCOHOL; TETRASODIUM EDTA; EUCALYPTUS GLOBULUS LEAF OIL; ALOE BARBADENSIS LEAF JUICE; SQUALANE; BORAGO OFFICINALIS SEED OIL; STEARYL ALCOHOL; CETEARETH-20

Methylten Cream

Active Ingredients:

Methyl Salicylate 10%

Purpose:

Topical Analgesic

Uses:

For the temporary relief of minor aches and pains of muscles and joints.

Warnings:

■ For External Use Only

KEEP OUT OF REACH OF CHILDREN

■ Keep this and all other drugs out of the reach of children.

When using this product

■ Avoid contact with eyes ■ Do not bandage tightly ■ Do not apply to wounds or broken skin ■ If condition worsens or if symptoms persist for more than 7 days or clear up and occur again within a few days, discontinue use of this product and consult a physician.

Stop use and ask doctor if

■ pain persists for more than 7 days, redness is present or in conditions affecting children under 12 years of age. ■ excessive irritation of the skin develops. ■ if pregnant or breastfeeding ■ ask a health professional before use.

Directions

■ Use only as directed. Adults and children 2 years and older: Apply to affected area no more than 3 to 4 times daily. ■ Children under 2 years of age: Do not use, consult a physician

Other information

■ store between 20° to 25° C (68°- 77° F)

Inactive ingredients:

Aloe Barbadensis (Aloe Vera) Leaf Juice, Aqua (Purified Water), Borago Officinalis (Borage) Seed Oil, Carbomer. Ceteareth-20, Cetearyl Alcohol, Cetyl Alcohol , Eucalyptus Globus Leaf Oil, Fructose, Phenoxyethanol, Propylene Glycol, Sodium Hydroxide, Squalane, Stearic Acid, Stearyl Alcohol, Tetrasodium EDTA, Tocopheryl Acetate, Vitis Vinifera (Grape) Seed Oil, Fragrance.

MethyltenTM

Manufactured by:
PureTek Corporation
Panorama City, CA 91402
For questions or information
call toll-free: 877-921-7873